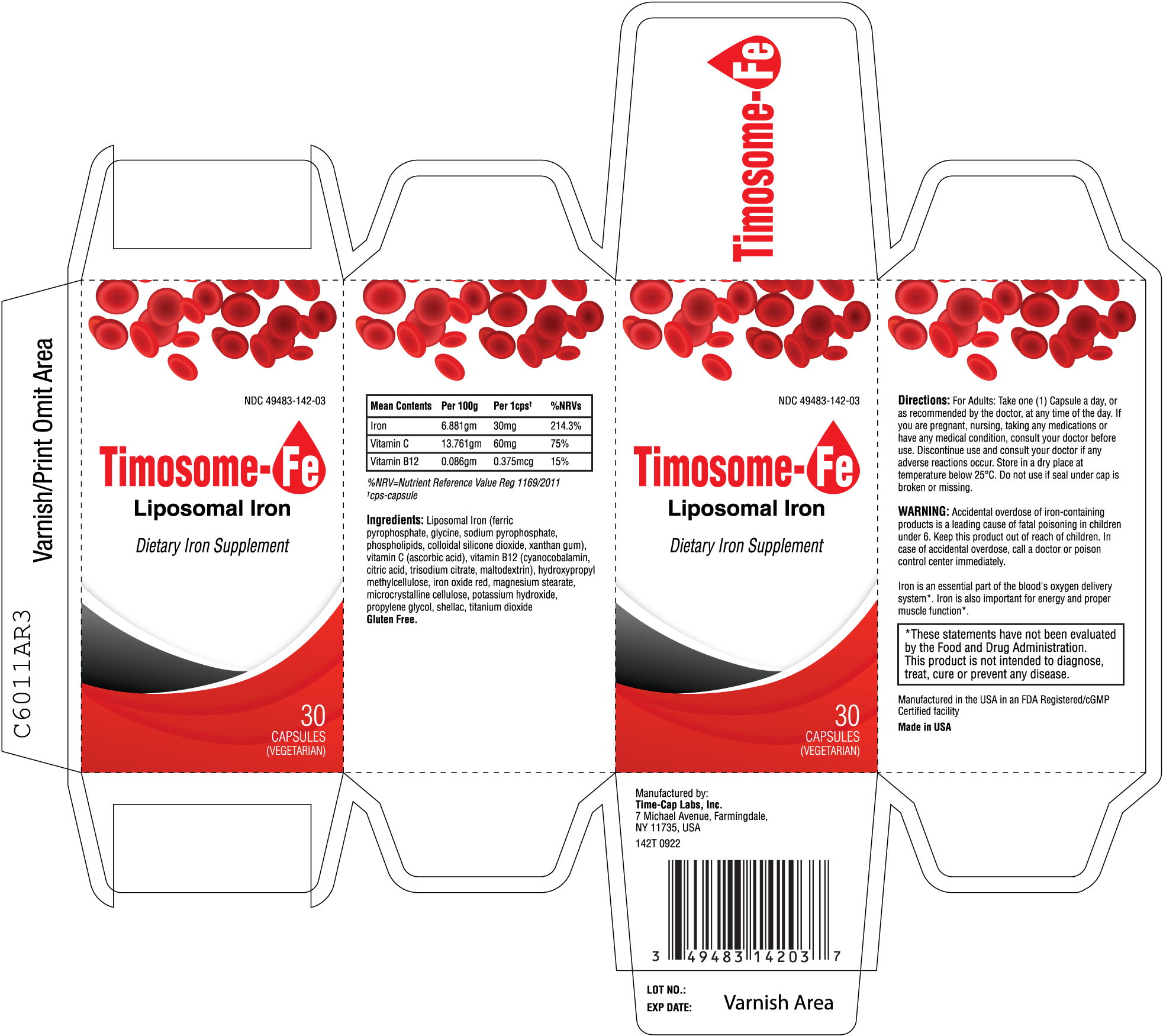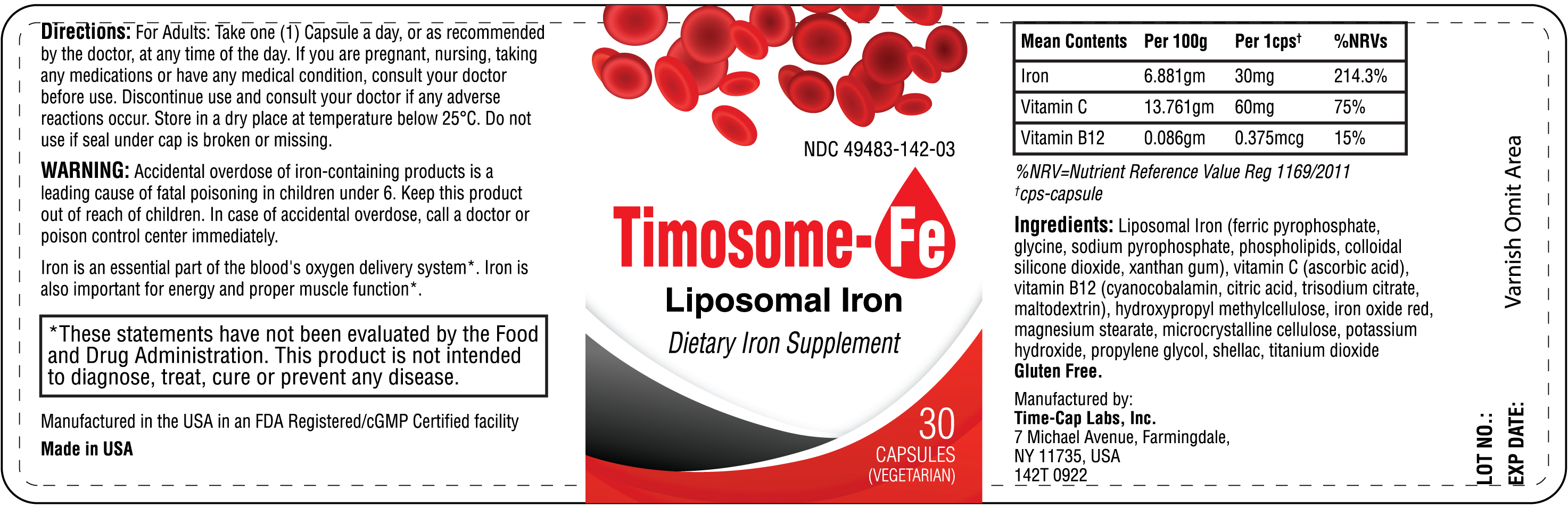 DRUG LABEL: Timosome Fe
NDC: 49483-142 | Form: CAPSULE
Manufacturer: TIME CAP LABORATORIES, INC.
Category: other | Type: Dietary Supplement
Date: 20221122

ACTIVE INGREDIENTS: FERRIC PYROPHOSPHATE 30 mg/1 1; ASCORBIC ACID 60 mg/1 1; CYANOCOBALAMIN 0.375 mg/1 1
INACTIVE INGREDIENTS: HYPROMELLOSE, UNSPECIFIED; FERRIC OXIDE RED; MAGNESIUM STEARATE; MICROCRYSTALLINE CELLULOSE; POTASSIUM HYDROXIDE; PROPYLENE GLYCOL; SHELLAC; TITANIUM DIOXIDE; GLYCINE; SODIUM PYROPHOSPHATE; LECITHIN, SOYBEAN; SILICON DIOXIDE; XANTHAN GUM; MALTODEXTRIN; SODIUM CITRATE, UNSPECIFIED FORM; CITRIC ACID MONOHYDRATE

142T Timely Timosome Fe Liposomal Iron supplement

STATEMENT OF IDENTITY

Liposomal Iron

Directions

Supplements Fact
Mean Contents | Per 100 g | Per 1 cps† | % NRVs
Iron | 6.881 gm | 30 mg | 214.3%
Vitamin C | 13.761 gm | 60 mg | 75%
Vitamin B12 | 0.086 gm | 0.375 mg | 15%

%NRV=Nutrient Reference Value Reg 1169/2011
†cps-capsule

Ingredients: Liposomal Iron (ferric pyrophosphate, glycine, sodium pyrophosphate, phospholipids, colloidal silicone dioxide, xanthan gum), vitamin C (ascorbic acid), vitamin B12 (cyanocobalamin, citric acid, trisodium citrate, maltodextrin), hydroxypropyl methylcellulose, iron oxide red, magnesium stearate, microcrystalline cellulose, potassium hydroxide, propylene glycol, shellac, titanium dioxide
Gluten Free.

For Adults: Take one (1) Capsule a day, or as recommended by the doctor, at any time of the day. If you are pregnant, nursing, taking any medications or have any medical condition, consult your doctor before use. Discontinue use and consult your doctor if any adverse reactions occur. Store in a dry place at temperature below 25°C. Do not use if seal under cap is broken or missing.

Warnings

Accidental overdose of iron-containing products is a leading cause of fatal poisoning in children under 6. Keep this product out of reach of children. In case of accidental overdose, call a doctor or poison control center immediately.

142T-Timely-TimosomeFe-30s-IFC

142T-Timely-TimosomeFe-30s-Label

PACKAGE LABEL

142T-Timely-TimosomeFe-30s-IFC

142T-Timely-TimosomeFe-30s-Label